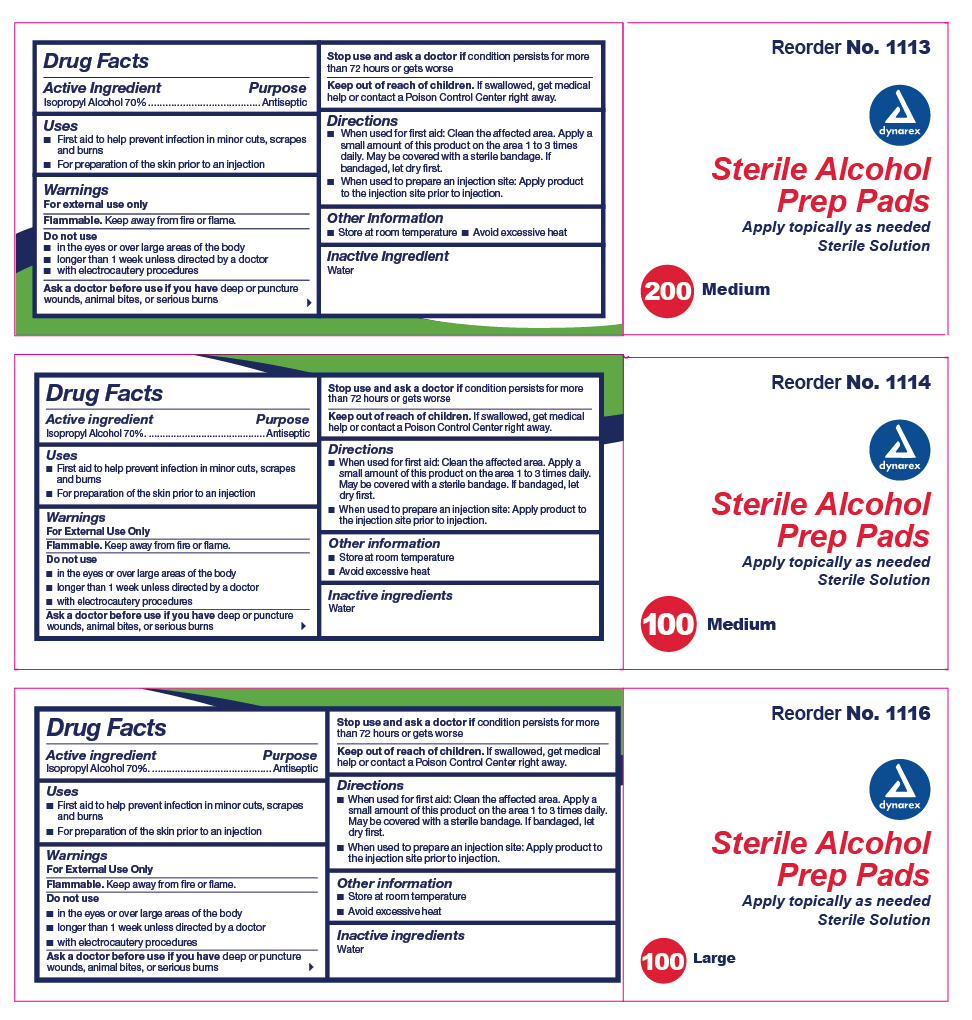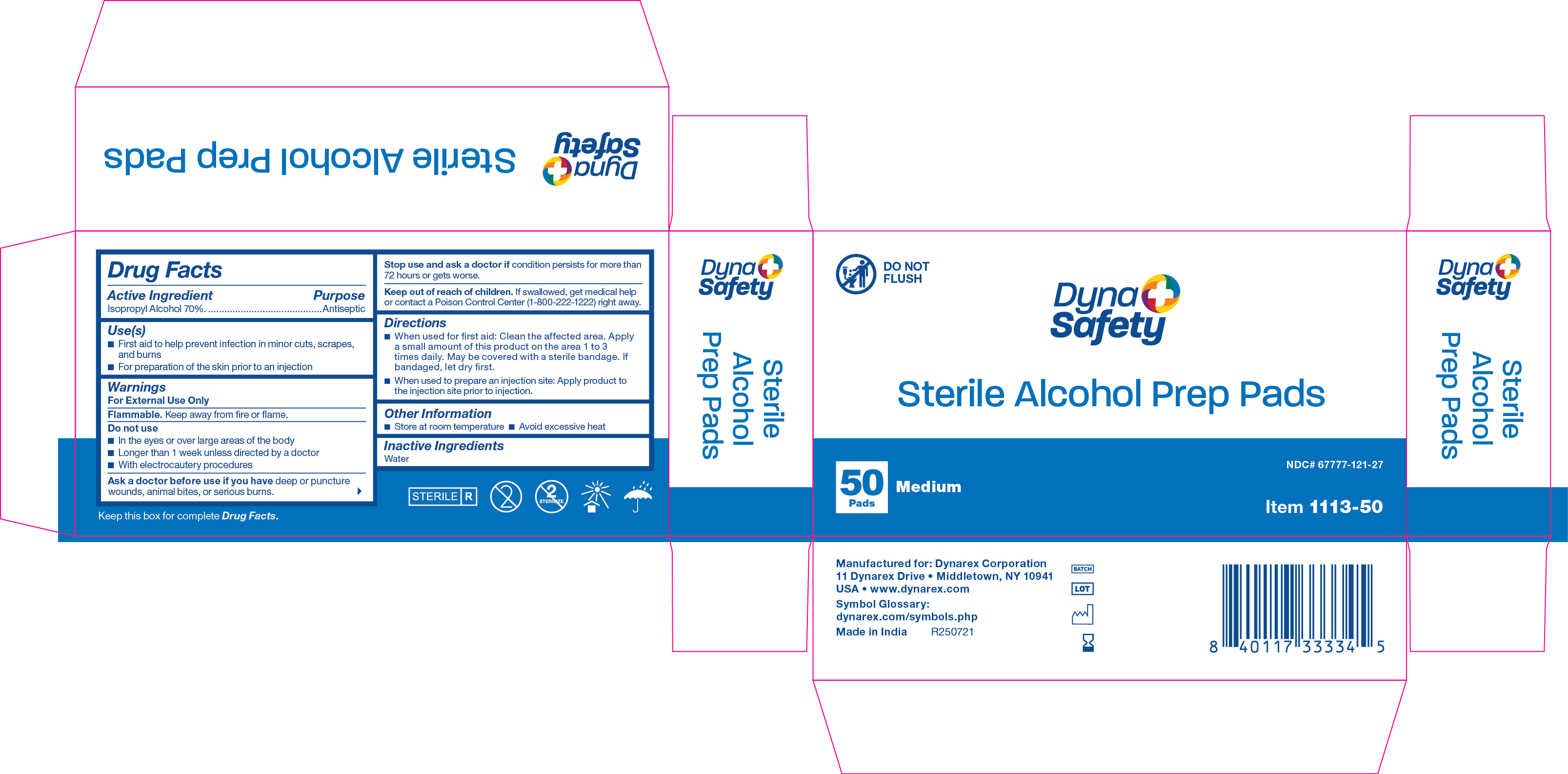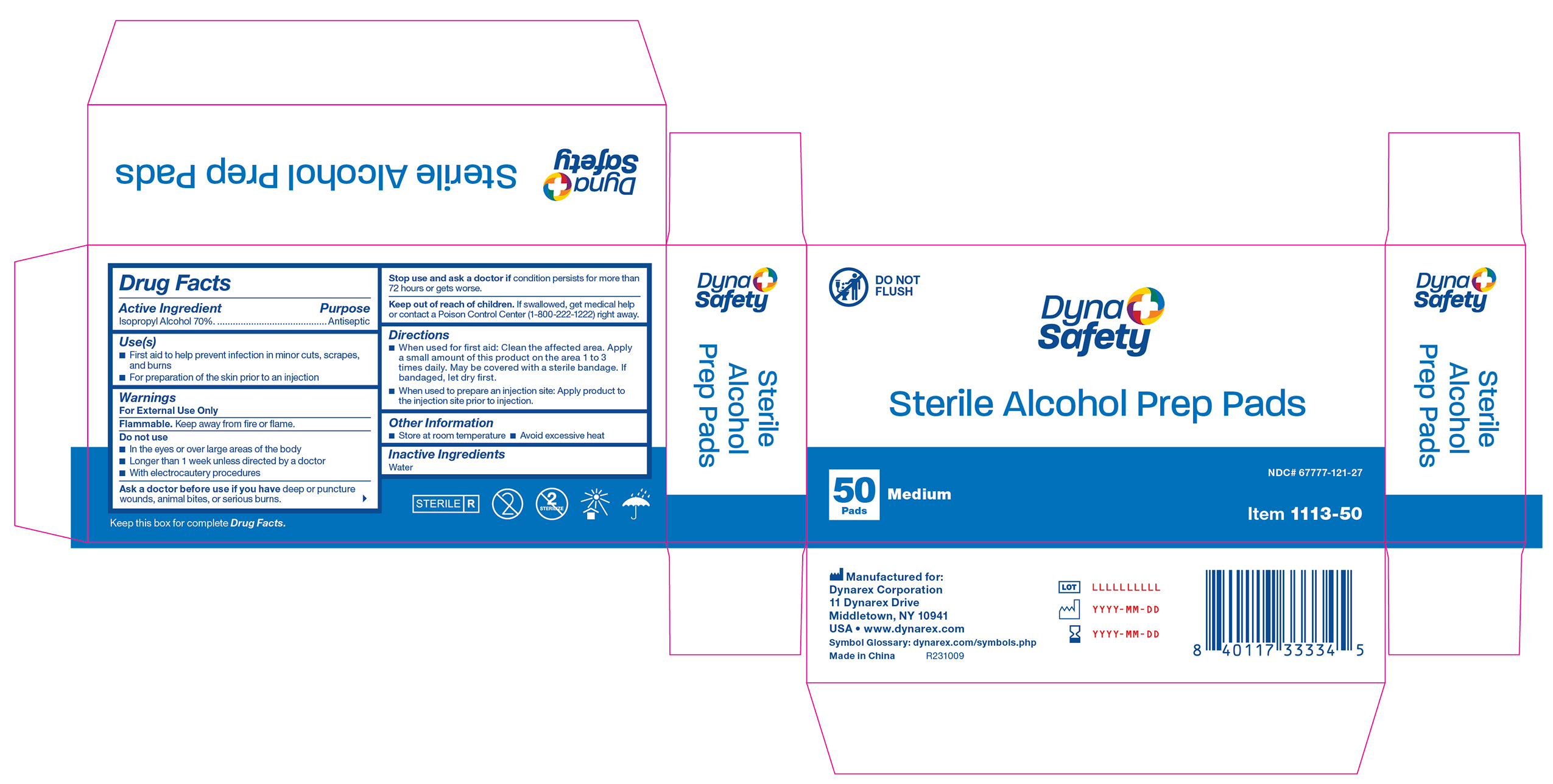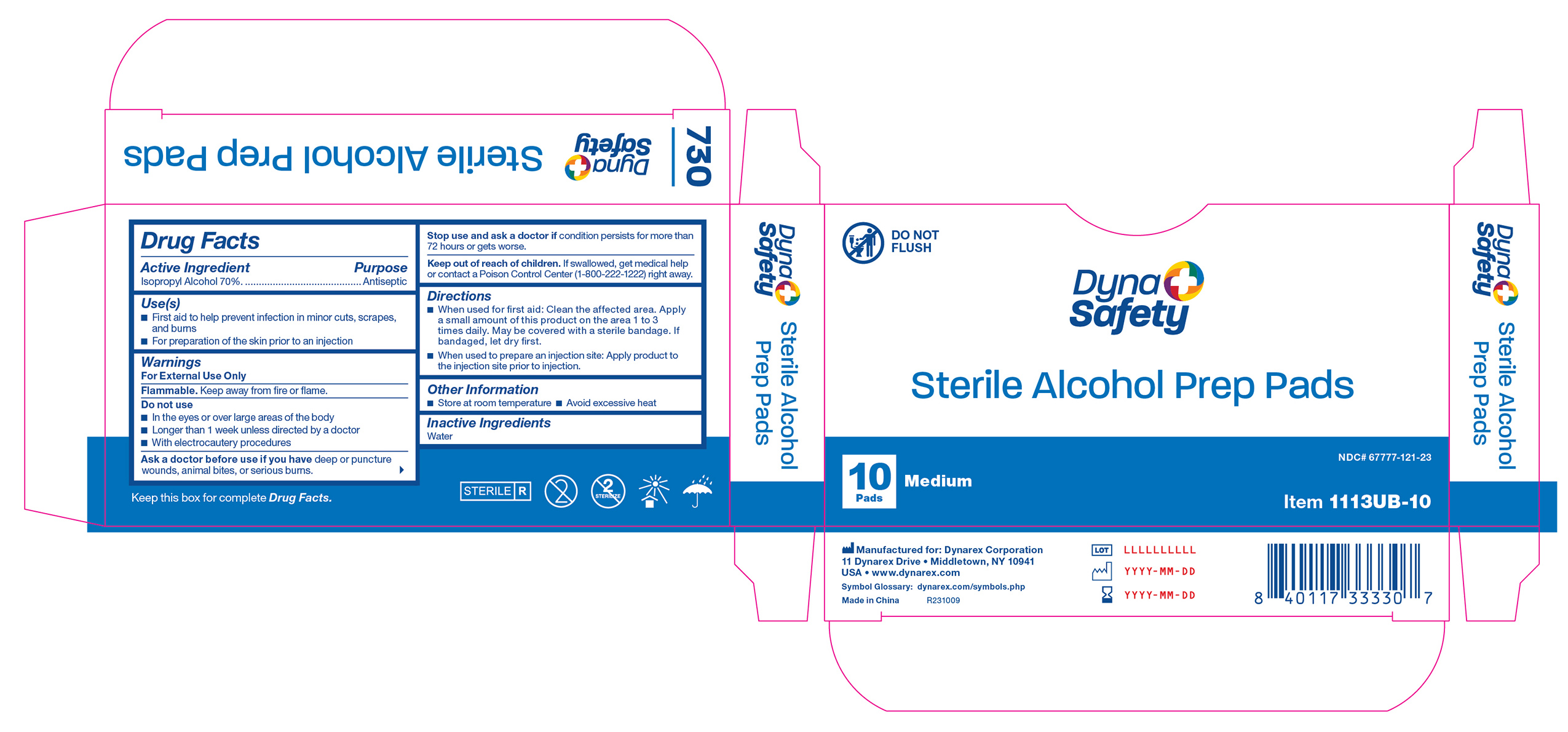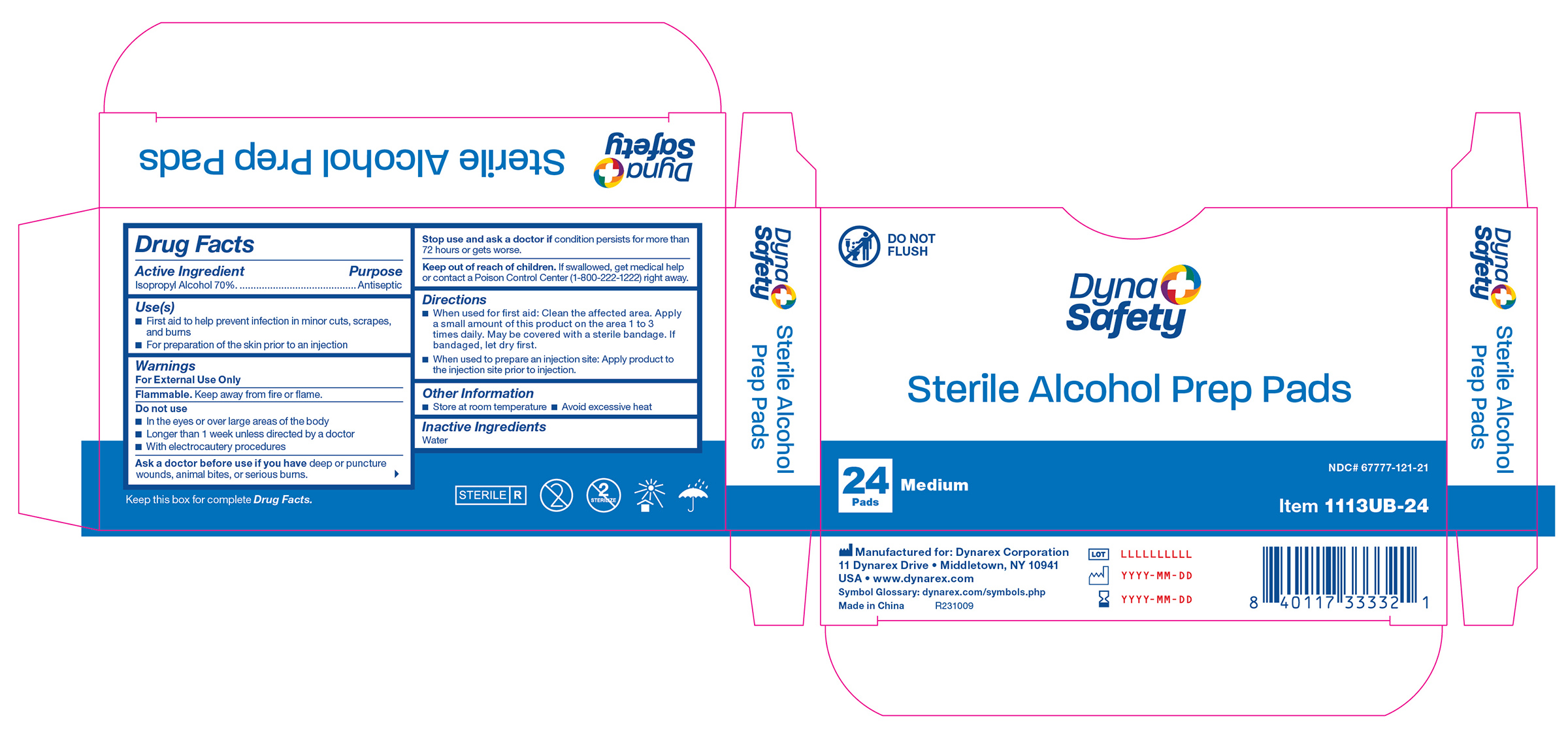 DRUG LABEL: Alcohol Prep
NDC: 67777-121 | Form: SWAB
Manufacturer: Dynarex Corporation
Category: otc | Type: HUMAN OTC DRUG LABEL
Date: 20251216

ACTIVE INGREDIENTS: ISOPROPYL ALCOHOL 0.7 mL/1 mL
INACTIVE INGREDIENTS: WATER

1113, 1114, 1116, 1113UB-24, 1113UB-10, 1113-50 Sterile Alcohol Prep Pads

Active Ingredient

Isopropyl Alcohol 70%

Purpose

Antiseptic

Use(s)

• First aid to help prevent infection in minor cuts, scrapes, and burns

• For preparation of the skin prior to an injection

Warnings

For External Use only

Flammable. Keep away from fire or flame.

Do not use

• In the eyes or over large areas of the body

• Longer than 1 week unless directed by a doctor

• With electrocautery procedures

Ask a doctor before use if you have

Deep or puncture wounds, animal bites, or serious burns.

Stop use and ask a doctor if

Condition persists for more than 72 hours or gets worse.

Keep out of reach of children

If swallowed, get medical help or contact a Poison Control Center (1-800-222-1222) right away.

Directions

• When used for first aid: Clean the affected area. Apply a small amount of this product on the area 1 to 3 times daily. May be covered with a sterile bandage. If bandaged, let dry first.

• When used to prepare an injection site: Apply product to the injection site prior to injection.

Other Information

- Store at room temperature
- Avoid excessive heat

Inactive Ingredient

Water

Label 1113-50

1113-50

Label 1113UB-24

1113UB-24

Label 1113UB-10

1113UB-10

Label 1113-50

1113-50 PHFL010